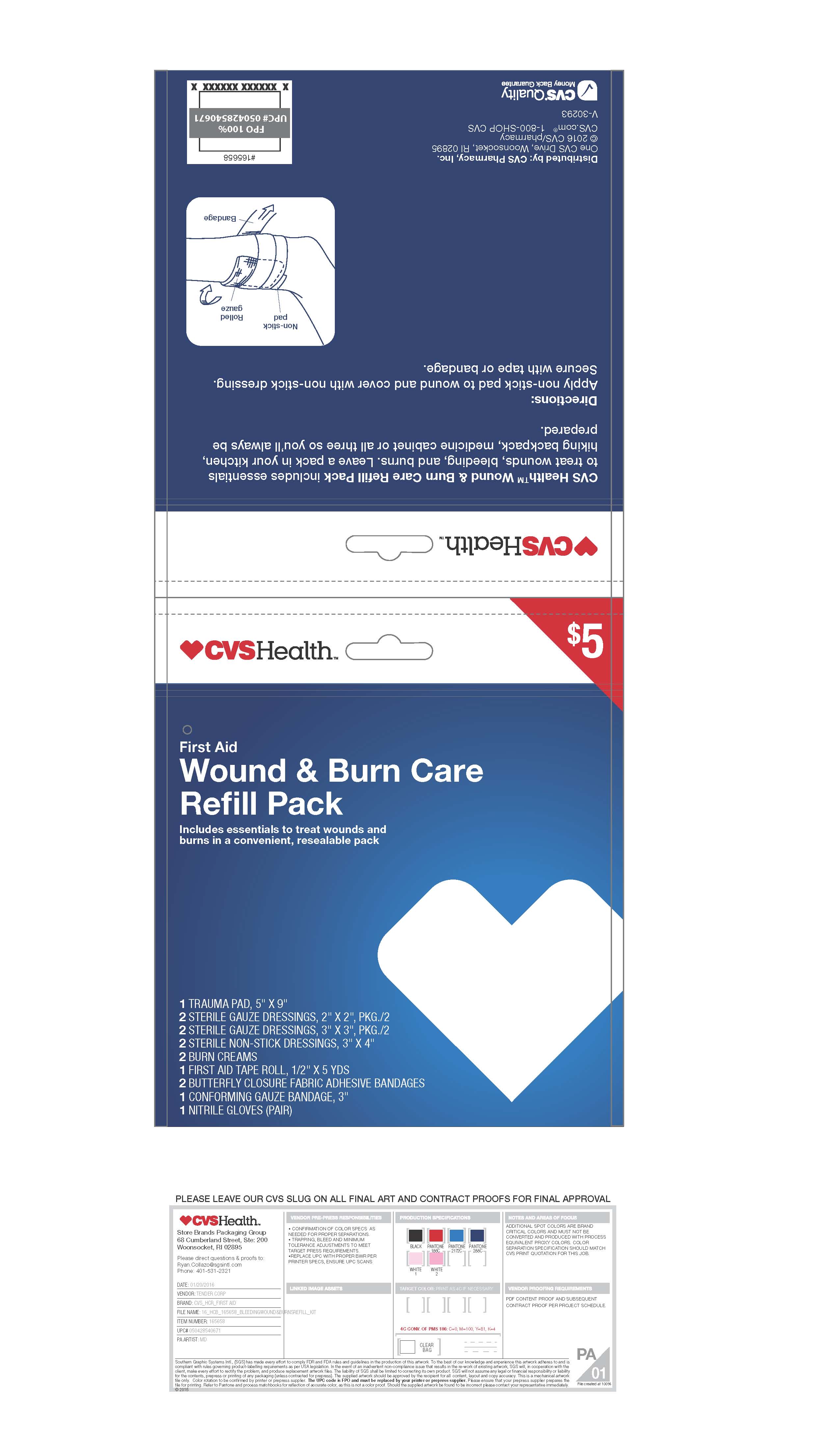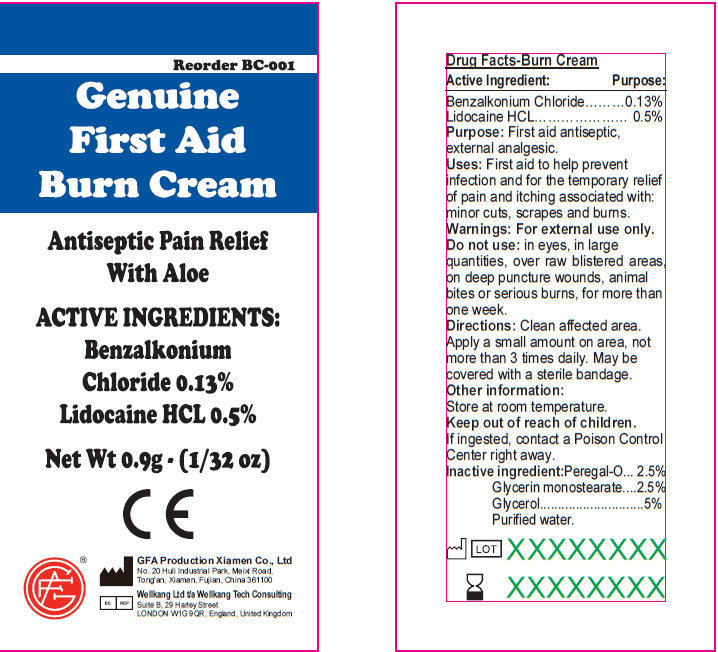 DRUG LABEL: Wound and Burn Care Refill Pack
NDC: 69842-401 | Form: KIT | Route: TOPICAL
Manufacturer: CVS
Category: otc | Type: HUMAN OTC DRUG LABEL
Date: 20161228

ACTIVE INGREDIENTS: BENZALKONIUM CHLORIDE 0.13 g/100 g; LIDOCAINE HYDROCHLORIDE 0.5 g/100 g
INACTIVE INGREDIENTS: POLYOXYL 20 CETOSTEARYL ETHER; GLYCERYL ISOSTEARATE; WATER; GLYCERIN

CVS Wound & Burn Care Refill Pack

Active Ingredients

Benzalkonium Chloride 0.13%
Lidocaine HCL 0.5%

Purpose

First aid antiseptic, external analgesic

Uses

First aid to help prevent infection and for the temporary relief of pain and itching associated with:

Minor Cuts

Scrapes

Burns

Warnings

For external use only

Do not use: In eyes, in large quantities, over raw blistered areas, or on deep puncture wounds, animal bites or serious burns, for more than one week
Do not use:
in the eyes or apply over large areas of the body.
longer than 1 week unless directed by a doctor.
in large quantities, particularly over raw surfaces or blistered areas.
Ask a doctor before use if you have deep puncture wounds, animal bites or serious burns.
When using this product, avoid contact with the eyes.

Stop Use

Stop use and ask a doctor if
condition worsens
symptoms persist for more than 7 days
condition clears up and occurs again within a few days

Keep Out of Reach of Children

If ingested, contact a Poison Control Center right away.

Directions

Adults and children 2 years of age and older

clean affected area.

apply a small amount of this product on the area 1 to 3 times daily.

may be covered with a sterile bandage

children under 2 years of age: consult a doctor

Storage and Handling

Other Information:
Store at room temperature (do not freeze).

Taper evident sealed packets.

Do not use packet if opened or torn.

Inactive Ingredients

Peregal-O

Glycerin monostearate

Glycerol

Purified Water.

PACKAGE LABEL

Genuine First Aid Burn Cream
Antiseptic Pain Relief With Aloe
Net Wt 0.9g (1/32 oz)
Manufactured in CHINA for
Genuine First Aid

GFA Production Xiamen Co., Ltd
No. 20 Huli Industrial Park, Meixi Road, Tong'an, Xiamen, Fujian, China 361100
Tel: 86-592-7269515 Fax: 86-592-7269528 Http: //www.gfaproduction.com